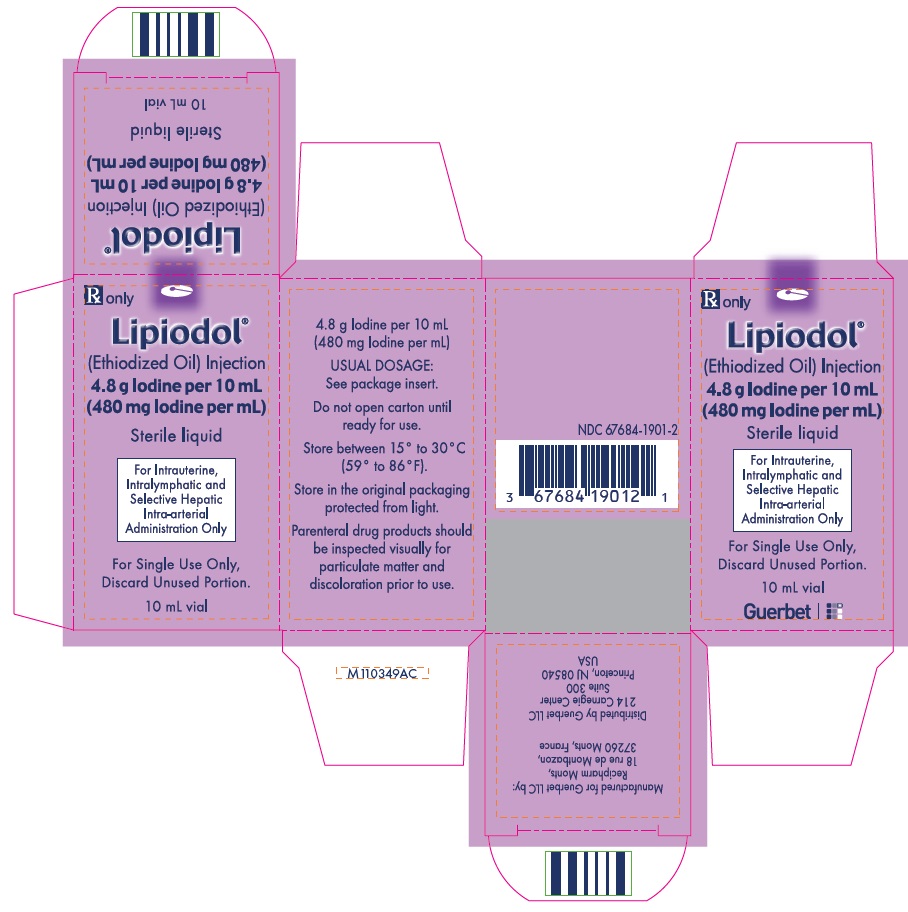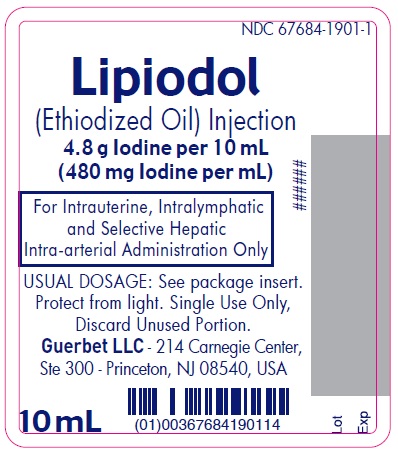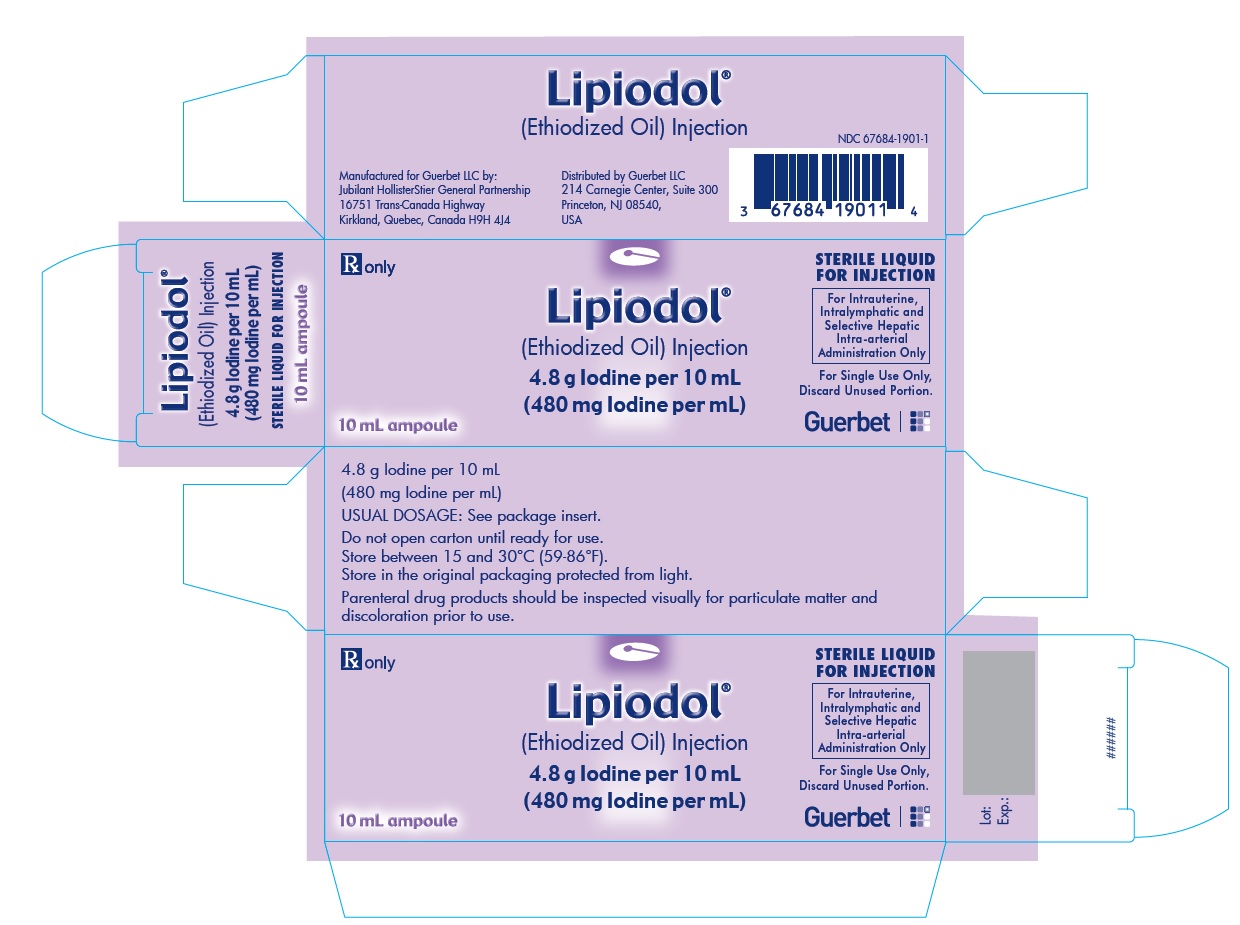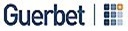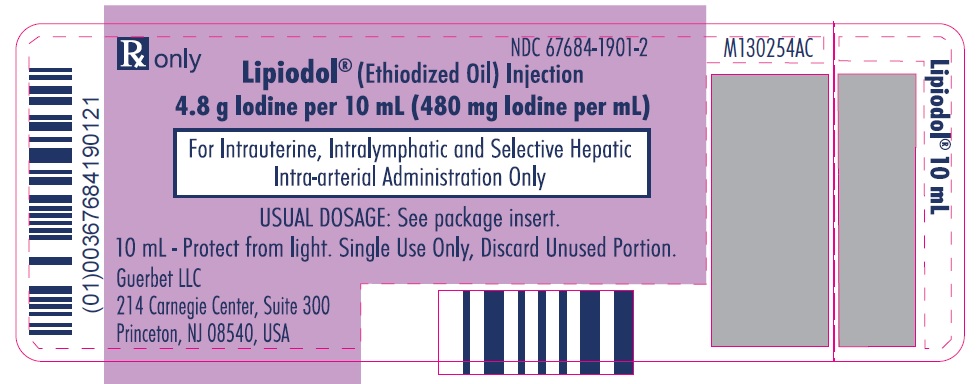 DRUG LABEL: LIPIODOL
NDC: 67684-1901 | Form: INJECTION
Manufacturer: Guerbet LLC
Category: prescription | Type: HUMAN PRESCRIPTION DRUG LABEL
Date: 20251216

ACTIVE INGREDIENTS: ETHIODIZED OIL 480 mg/1 mL
INACTIVE INGREDIENTS: POPPY SEED OIL

HIGHLIGHTS OF PRESCRIBING INFORMATION

These highlights do not include all the information needed to use LIPIODOL safely and effectively. See full prescribing information for LIPIODOL.
LIPIODOL® (Ethiodized Oil) Injection, for intrauterine, intralymphatic, or intra-arterial use
Initial U.S. Approval: 1954

BOXED WARNING

WARNING: FOR INTRALYMPHATIC, INTRAUTERINE AND SELECTIVE HEPATIC INTRA-ARTERIAL USE ONLY
See Full Prescribing Information for complete Boxed Warning
Pulmonary and cerebral embolism can result from inadvertent intravascular injection or intravasation of Lipiodol. Inject Lipiodol slowly with radiologic monitoring; do not exceed recommended dose (5.1).

1 INDICATIONS AND USAGE

Lipiodol is an oil-based radiopaque contrast agent indicated for:

- hysterosalpingography in adults
- lymphography in adult and pediatric patients
- selective hepatic intra-arterial use for imaging tumors in adults with known hepatocellular carcinoma (HCC)

2 DOSAGE AND ADMINISTRATION

Use a disposable syringe to draw and inject Lipiodol.

- Hysterosalpingography
  Inject increments of 2 mL of Lipiodol into the endometrial cavity until tubal patency is determined; stop the injection if the patient develops excessive discomfort. Inject with radiologic monitoring.
- Lymphography
  Inject Lipiodol into a lymphatic vessel with radiologic monitoring.
  Adults:
- unilateral lymphography of the upper extremities: 2 to 4 mL
- unilateral lymphography of the lower extremities: 6 to 8 mL
- penile lymphography: 2 to 3 mL
- cervical lymphography: 1 to 2 mL
  Pediatric patients:
- Inject a minimum of 1 mL to a maximum of 6 mL according to the anatomical area to be visualized. Do not exceed 0.25 mL/kg.
- Selective Hepatic Intra-arterial Use
  Inject 1.5 to 15 mL of Lipiodol slowly under continuous radiologic monitoring. Do not exceed 20 mL total dosage.

3 DOSAGE FORMS AND STRENGTHS

Each mL of Lipiodol contains 480 mg Iodine organically combined with ethyl esters of fatty acids of poppy seed oil.

4 CONTRAINDICATIONS

Hypersensitivity to Lipiodol, hyperthyroidism, traumatic injuries, recent hemorrhage or bleeding.

- Lipiodol Hysterosalpingography is contraindicated in:
  pregnancy, acute pelvic inflammatory disease, marked cervical erosion, endocervicitis and intrauterine bleeding, in the immediate pre-or postmenstrual phase, and within 30 days of curettage or conization or patients with known or suspected reproductive tract neoplasia due to the risk of peritoneal spread of neoplasm.
- Lipiodol Lymphography is contraindicated in:
  right to left cardiac shunt, advanced pulmonary disease, tissue trauma or hemorrhage, advanced neoplastic disease with expected lymphatic obstruction, previous surgery interrupting the lymphatic system, or radiation therapy to the examined area.
- Lipiodol Selective Hepatic Intra-arterial Injection is contraindicated in:
  the presence of dilated bile ducts unless external biliary drainage was performed before injection.

5 WARNINGS AND PRECAUTIONS

- Pulmonary and cerebral embolism: avoid use in patients with severely impaired lung function, cardiorespiratory failure or right-sided cardiac overload (5.1)
- Hypersensitivity reactions: avoid use in patients with a history of sensitivity to other iodinated contrast agents, bronchial asthma or allergic disorders because of an increased risk of a hypersensitivity reaction to Lipiodol (5.2)
- Exacerbation of chronic liver disease (5.3)
- Thyroid dysfunction (5.4)

6 ADVERSE REACTIONS

Adverse reactions caused by Lipiodol include hypersensitivity reactions, pulmonary embolism, pulmonary dysfunction, exacerbation of liver disease, procedural complications, abdominal pain, fever, nausea, vomiting, and thyroid dysfunction.

To report SUSPECTED ADVERSE REACTIONS, contact GUERBET LLC at 1-877-729-6679 or FDA at 1-800-FDA-1088 or www.fda.gov/medwatch

7 DRUG INTERACTIONS

Lipiodol may interfere with thyroid function testing and with radioactive iodine uptake by the thyroid tissue during diagnostic or therapeutic procedures. (7.1)

8 USE IN SPECIFIC POPULATIONS

- Pregnancy:Consider thyroid function testing in pregnant women and their infants if exposed to Lipiodol either before or during pregnancy, if clinically indicated (8.1)
- Lactation:Consider thyroid function testing in a breastfed infant whose mother was exposed to Lipiodol or, if clinically indicated (8.2)

RECENT MAJOR CHANGES

Contraindications (4) 11/2022

Warnings and Precautions, Thyroid Dysfunction (5.4) 4/2022

FULL PRESCRIBING INFORMATION

BOXED WARNING

WARNING: FOR INTRALYMPHATIC, INTRAUTERINE AND SELECTIVE HEPATIC INTRA-ARTERIAL USE ONLY

Pulmonary and cerebral embolism can result from inadvertent intravascular injection or intravasation of Lipiodol.
Inject Lipiodol slowly with radiologic monitoring; do not exceed recommended dose (5.1).

1 INDICATIONS AND USAGE

Lipiodol is an oil-based radio-opaque contrast agent indicated for:

- hysterosalpingography in adults
- lymphography in adult and pediatric patients
- selective hepatic intra-arterial use for imaging tumors in adults with known hepatocellular carcinoma (HCC)

2 DOSAGE AND ADMINISTRATION

2.1 Dosing Guidelines

Draw Lipiodol into a disposable syringe.
Use the smallest possible amount of Lipiodol according to the anatomical area to be visualized.

Hysterosalpingography

Using aseptic technique inject Lipiodol into the endometrial cavity with fluoroscopic control. Inject increments of 2 mL of Lipiodol until tubal patency is determined; stop the injection if patient develops excessive discomfort. The total volume to be injected depends on the
volume of the uterine cavity, usually not exceeding 15 mL. A 24-hour image can be obtained if, after slow peritoneal spillage, the evaluation of adhesions is needed. Perform the procedure during the follicular phase of the menstrual cycle.

Before using Lipiodol exclude the presence of these conditions: pregnancy, uterine bleeding and endocervicitis, acute pelvic inflammatory disease, the immediate pre-or postmenstrual phase or within 30 days of curettage or conization. [see Contraindications (4) & Pregnancy (8.1) ].

Lymphography

Inject Lipiodol into a lymphatic vessel under radiologic guidance to prevent inadvertent venous administration or intravasation.

Adults:

- unilateral lymphography of the upper extremities 2 to 4 mL
- unilateral lymphography of the lower extremities 6 to 8 mL
- penile lymphography 2 to 3 mL
- cervical lymphography 1 to 2 mL

Pediatric patients:

- Inject a minimum of 1 mL to a maximum of 6 mL according to the anatomical area to be visualized. Do not exceed 0.25 mL/kg.

The following method is recommended for lymphography of the upper or lower extremities. Start the injection of Lipiodol into a lymphatic channel at a rate not to exceed 0.2 mL per minute. Inject the total dose of Lipiodol in no less than 1.25 hours. Use frequent radiologic monitoring to determine the appropriate injection rate and to follow the progress of Lipiodol within the lymphatics. Interrupt the injection if the patient experiences pain. Terminate the injection if lymphatic blockage is present to minimize introduction of Lipiodol into the venous circulation via lymphovenous channels. Terminate the injection as soon as Lipiodol is radiographically evident in the thoracic duct to minimize entry of Lipiodol into the subclavian vein and pulmonary embolization. Obtain immediate post-injection images. Re-image at 24 or 48 hours to evaluate nodal architecture.

Selective Hepatic Intra-arterial Injection

Determine the dose depending on the tumor size, local blood flow in the liver and in the tumor(s).

- Inject from 1.5 to 15 mL slowly under continuous radiologic monitoring. Stop the injection when stagnation or reflux is evident. Limit the dose to only the quantity required for adequate visualization. The total dose of Lipiodol administered should not exceed 20 mL.

2.2 Drug Handling

Inspect Lipiodol visually for particulate matter and discoloration before administration. Do not use the solution if particulate matter is present or if the container appears damaged. Lipiodol is a clear, pale yellow to amber colored oil; do not use if the color has darkened.

Draw Lipiodol into a disposable syringe and use promptly. Discard any unused portion of Lipiodol.

3 DOSAGE FORMS AND STRENGTHS

Each milliliter of Lipiodol contains 480 mg/mL of Iodine organically combined with ethyl esters of fatty acids of poppy seed oil.

4 CONTRAINDICATIONS

Lipiodol is contraindicated in patients with hypersensitivity to Lipiodol, hyperthyroidism, traumatic injuries, recent hemorrhage or bleeding.

Hysterosalpingography

Lipiodol hysterosalpingography is contraindicated in pregnancy, acute pelvic inflammatory disease, marked cervical erosion, endocervicitis and intrauterine bleeding, in the immediate pre-or postmenstrual phase, and within 30 days of curettage or conization or patients with known or suspected reproductive tract neoplasia due to the risk of peritoneal spread of neoplasm. [see Use in Specific Populations (8.1) .]

Lymphography

Lipiodol Lymphography is contraindicated in patients with a right to left cardiac shunt, advanced pulmonary disease, tissue trauma or hemorrhage advanced neoplastic disease with expected lymphatic obstruction, previous surgery interrupting the lymphatic system, radiation therapy to the examined area.

Selective Hepatic Intra-arterial Use Patients with HCC

Lipiodol use is contraindicated in areas of the liver where the bile ducts are dilated unless external biliary drainage was performed before injection.

5 WARNINGS AND PRECAUTIONS

5.1 Pulmonary and Cerebral Embolism

Pulmonary embolism may occur immediately or after a few hours to days from inadvertent systemic vascular injection or intravasation of Lipiodol and cause decreased pulmonary diffusing capacity and pulmonary blood flow, pulmonary infarction, acute respiratory distress syndrome and fatalities. Embolization of Lipiodol to brain and other major organs may occur. Avoid use of Lipiodol in patients with severely impaired lung function, cardiorespiratory failure, or right–sided cardiac overload. Perform radiological monitoring during the Lipiodol injection. Do not exceed the recommended maximum dose and rate of injection of Lipiodol. During lymphography to minimize the risk of pulmonary embolism obtain radiographic confirmation of intralymphatic (rather than venous) injection, and terminate the procedure when Lipiodol becomes visible in the thoracic duct or lymphatic obstruction is observed.

5.2 Hypersensitivity Reactions

Anaphylactoid and anaphylactic reactions with cardiovascular, respiratory or cutaneous manifestations, ranging from mild to severe, including death, have uncommonly occurred following Lipiodol administration. Avoid use in patients with a history of sensitivity to other iodinated contrast agents, bronchial asthma or allergic disorders because of an increased risk of a hypersensitivity reaction to Lipiodol. Administer Lipiodol only in situations where trained personnel and therapies are promptly available for the treatment of hypersensitivity reactions, including personnel trained in resuscitation; ensure continuous medical monitoring and maintain an intravenous access line. Most hypersensitivity reactions to Lipiodol occur within half an hour after administration. Delayed reactions can occur up to several days after administration. Observe patients for signs and symptoms of hypersensitivity reactions during and for at least 30 minutes following Lipiodol administration.

5.3 Exacerbation of Chronic Liver Disease

Lipiodol hepatic intra-arterial administration can exacerbate the following conditions: portal hypertension and cause variceal bleeds due to obstruction of the intrahepatic portal channels by opening a pre sinusoidal anastomosis; hepatic ischemia and cause liver enzyme elevations, fever and abdominal pain; hepatic failure and cause ascites and encephalopathy. Hepatic vein thrombosis, irreversible liver insufficiency and fatalities have been reported. Procedural risks include vascular complications and infections.

5.4 Thyroid Dysfunction

Iodinated contrast media can affect thyroid function because of the iodide content and can cause hyperthyroidism or hypothyroidism. Ethiodized oil may remain in the body for several months, depending on dose administered and route of administration. Keep the dose of Lipiodol as low as possible and consider monitoring thyroid function closely for several months after administration of Lipiodol.

6 ADVERSE REACTIONS

6.2 Postmarketing Experience

The following adverse reactions (Table 1) have been identified during post approval use of Lipiodol. Because these reactions are reported voluntarily from a population of uncertain size, it is not always possible to reliably estimate their frequency or establish a causal relationship to drug exposure.

The following adverse reactions are described in more detail in other sections of the prescribing information:
Pulmonary and cerebral embolism [see Warnings and Precautions (5.1) ]
Hypersensitivity reactions [see Warnings and Precautions (5.2) ]
Exacerbation of chronic liver disease [see Warnings and Precautions (5.3) ]

Thyroid dysfunction [see Warnings and Precautions (5.4) ]. Thyroid dysfunction in the mother and the infant of a subsequent pregnancy
[See Use in Specific Populations (8.1)]

Table 1: Adverse Reactions in the Postmarketing Experience
System Organ Class | Adverse Reaction
Eye disorders | retinal vein thrombosis
General disorders and administration site conditions | fever, pain, granuloma
Immune system disorders | hypersensitivity, anaphylactic reaction, anaphylactoid reaction, cardiovascular reactions
Nervous system disorders | cerebral embolism
Respiratory, thoracic and mediastinal disorders | pulmonary embolism, dyspnea, cough, acute respiratory distress syndrome
Urinary system disorders | renal insufficiency

Hysterosalpingography

Abdominal pain, foreign body reactions, exacerbation of pelvic inflammatory disease, salpingitis or pelvic peritonitis have been reported
after the examination in case of latent infection.

Lymphography

Lymphangitis, thrombophlebitis, edema or exacerbation of preexisting lymphedema, dyspnea and cough, iodism (headache, soreness of mouth and pharynx, coryza and skin rash), allergic dermatitis, lipogranuloma, delayed healing at the site of incision.

Selective Hepatic Intra-arterial Injection

Abdominal pain, nausea, and vomiting are the most common reactions; other reactions include hepatic vein thrombosis, hepatic ischemia, liver enzymes abnormalities, transitory decrease in liver function, liver decompensation and renal insufficiency. Procedural risks include vascular complications and infections.

7 DRUG INTERACTIONS

7.1 Interference with Iodine-Based Diagnostic Tests and Iodine-Based Radiotherapy

Following Lipiodol administration, ethiodized oil remains in the body for several months. Ethiodized oil interferes with radioactive iodine uptake by the thyroid for several weeks to months may impair visualization of thyroid scintigraphy and reduce effectiveness of iodine 131 treatment.

8 USE IN SPECIFIC POPULATIONS

8.1 Pregnancy

Risk Summary

Hysterosalpingography is contraindicated in pregnant women due to the potential risk to the fetus from an intrauterine procedure [see
Contraindications (4) ]. The use of Lipiodol before or during pregnancy may interfere with thyroid function in both the pregnant woman
and her fetus and may affect fetal development. There are maternal, fetal, and neonatal clinical considerations for women who are exposed to Lipiodol either before or during pregnancy (see Clinical Considerations). Rare pregnancy outcomes reported in the post marketing setting with Lipiodol use in pregnant women are insufficient to evaluate for a drug-associated risk of major birth defects or miscarriage (see Data). Animal reproduction studies have not been conducted using the indicated routes of administration of Lipiodol, it was not embryotoxic or teratogenic in animal studies with oral administration.

The estimated background risk of major birth defects and miscarriage for the indicated population is unknown. All pregnancies have a
background risk of major birth defects, loss, or other adverse outcomes. In the U.S. general population, the estimated background risk of
major birth defects and miscarriages in clinically recognized pregnancies is 2-4% and 15-20%, respectively.

Clinical Considerations

Maternal adverse reactions
The use of Lipiodol before or during pregnancy may interfere with the thyroid function of the pregnant woman. Untreated hypothyroidism in pregnancy is associated with adverse perinatal outcomes, such as spontaneous abortion, preeclampsia, preterm birth, abruptio placentae, and fetal death. Consider thyroid function testing during pregnancy if a woman was exposed to Lipiodol either before or during pregnancy or if clinically indicated [see Warnings and Precautions (5.4) ].

Fetal / Neonatal adverse reactions
The use of Lipiodol before or during pregnancy causes iodide transfer across the placenta which may interfere with fetal thyroid function
and may affect fetal development. Untreated hypothyroidism is associated with increased fetal risk of low birth weight, fetal distress, and
impaired neuropsychological development. Consider thyroid function testing in infants whose mothers were exposed to Lipiodol before
and during pregnancy or if clinically indicated [see Warnings and Precautions (5.4) ].

Data

Human Data
In a prospective study, twenty-two euthyroid women with infertility underwent hysterosalpingography, and thyroid stimulating hormone,
serum iodine concentration, and urinary iodide/creatine excretion were evaluated at 4, 8, 12, 24 weeks. Six patients were followed upto12 months. The median value of urinary iodide excretion peaked at four weeks post-procedure and remained elevated at 8, 12, 24 weeks post-procedure compared to pre-procedure. Three patients showed elevated TSH (5 uIU/L) with normal T4 at 4 or 8 weeks after
hysterosalpingography.

In addition, there are post marketing reports of goiters and hypothyroidism in fetuses and infants whose mothers were exposed to Lipiodol for hysterosalpingography prior to pregnancy.

Animal Data
Lipiodol was not embryotoxic or teratogenic in rats after oral administration of up to 250 mg Iodine/kg each day between gestation days 6 to 17, or in rabbits after 4-5 intermittent (once every three days) oral administrations of 12.5 mg Iodine/kg between gestation days 6 to 18. Maternal
toxicity was observed in rats at 250 mg Iodine/kg/day.

8.2 Lactation

Risk Summary

Ethiodized oil is present in human milk.

There are no data on the effects of ethiodized oil on the breastfed infant, or effects on milk production, however, the use of Lipiodol may
increase the concentration of iodide in human milk and may interfere with the thyroid function of the breastfed infant. Consider thyroid
function testing in a breastfed infant whose mother was exposed to Lipiodol or if clinically indicated. The developmental and health
benefits of breastfeeding should be considered along with the mother’s clinical need for Lipiodol and any potential adverse effects on the
breastfed child from Lipiodol or from the underlying maternal condition.

8.3 Females and Males of Reproductive potential

Pregnancy Testing

Confirm that the patient has a negative pregnancy test within 24 hours before Lipiodol administration for hysterosalpingography [see
Dosage and Administration (2.1), Contraindications (4) ].

8.4 Pediatric Use

For lymphography use a dose of minimum of 1 mL to a maximum of 6 mL according to the anatomical area to be visualized. Do not exceed 0.25 mL/kg. Administer the smallest possible amount of Lipiodol according to the anatomical area to be visualized.

8.5 Geriatric Use

There are no studies conducted in geriatric patients.

8.6 Renal Impairment

Prior to an intra-arterial administration of Lipiodol screen all patients for renal dysfunction by obtaining history and/or laboratory tests.
Consider follow-up renal function assessments for patients with a history of renal dysfunction.

10 OVERDOSAGE

Overdose may lead to respiratory, cardiac or cerebral complications, which can potentially be fatal. Microembolisms to multiple organs may occur more frequently after overdose. Promptly initiate symptomatic treatment and support of vital functions.

11 DESCRIPTION

Lipiodol, ethiodized oil injection, is a sterile injectable radio-opaque agent. Each milliliter contains 480 mg of Iodine organically combined with ethyl esters of fatty acids of poppy seed oil. The precise structure of Lipiodol is unknown.

Lipiodol is a sterile, clear, pale yellow to amber colored oil. Lipiodol has a viscosity of 34 – 70 mPa·s at 20°C, and a density of 1.28 g/cm^3at 20°C.

12 CLINICAL PHARMACOLOGY

12.1 Mechanism of Action

Lipiodol opacifies vessels and body structures in the path of the flow of the contrast medium, permitting visualization of the internal structures.

12.2 Pharmacodynamics

Following administration of Lipiodol, the degree of enhancement is directly related to the local iodine content in the body structures to be imaged.

12.3 Pharmacokinetics

Following intra-arterial administration of Lipiodol, ethiodized oil retained in normal hepatic parenchyma is phagocytized by the Kupffer cells of the liver and washed out via the hepatic lymphatic system in about 2 to 4 weeks. In HCC, retention in the liver tumor is prolonged, allowing re-imaging of the tumor for four weeks or longer.

13 NONCLINICAL TOXICOLOGY

13.1 Carcinogenesis, Mutagenesis, Impairment of Fertility

Long-term studies in animals have not been performed to evaluate carcinogenic potential. Lipiodol did not demonstrate mutagenic potential in bacterial reverse mutation assays (in vitro), in a chromosomal aberration test in the mouse lymphoma assay (in vitro), and was negative in an in vivo micronucleus test in rats after intravenous injection of 479 mg I/kg.

16 HOW SUPPLIED/STORAGE AND HANDLING

Lipiodol is supplied in a box of one 10 mL ampoule, NDC 67684-1901-1.

Lipiodol is supplied in a box of one 10 mL vial, NDC 67684-1901-2.
Each vial is closed with a rubber stopper and sealed with an aluminum cap.

Store at controlled room temperature 15°-30°C (59°-86°F) [see USP, Controlled Room Temperature (CRT)]. Protect from light. Remove from carton only upon use.

17 PATIENT COUNSELING INFORMATION

Hypersensitivity Reactions

Advise the patient concerning the risk of hypersensitivity reactions that can occur both during and after Lipiodol administration. Advise
the patient to report any signs or symptoms of hypersensitivity reactions during the procedure and to seek medical attention for signs or
symptoms experienced after discharge [see Warnings and Precautions (5.2)] .

Thyroid Dysfunction

Advise patients concerning the risk of hyper- or hypothyroidism flowing the use of Lipiodol due to ethiodized oil remaining in the body
for several months. Instruct patients to follow up with their physician if they become pregnant or develop any signs of thyroid dysfunction in the months after administration [see Warnings and Precautions (5.4), Use in Specific Populations (8.1and 8.3)] .

Distributed by Guerbet LLC

214 Carnegie Center, Suite 300
Princeton, NJ 08540, USA

For further information or ordering, call

1-877-729-6679

Ampoules manufactured for Guerbet LLC by:

Jubilant HollisterStier General Partnership, Canada

Vials manufactured for Guerbet LLC by: Recipharm Monts, France